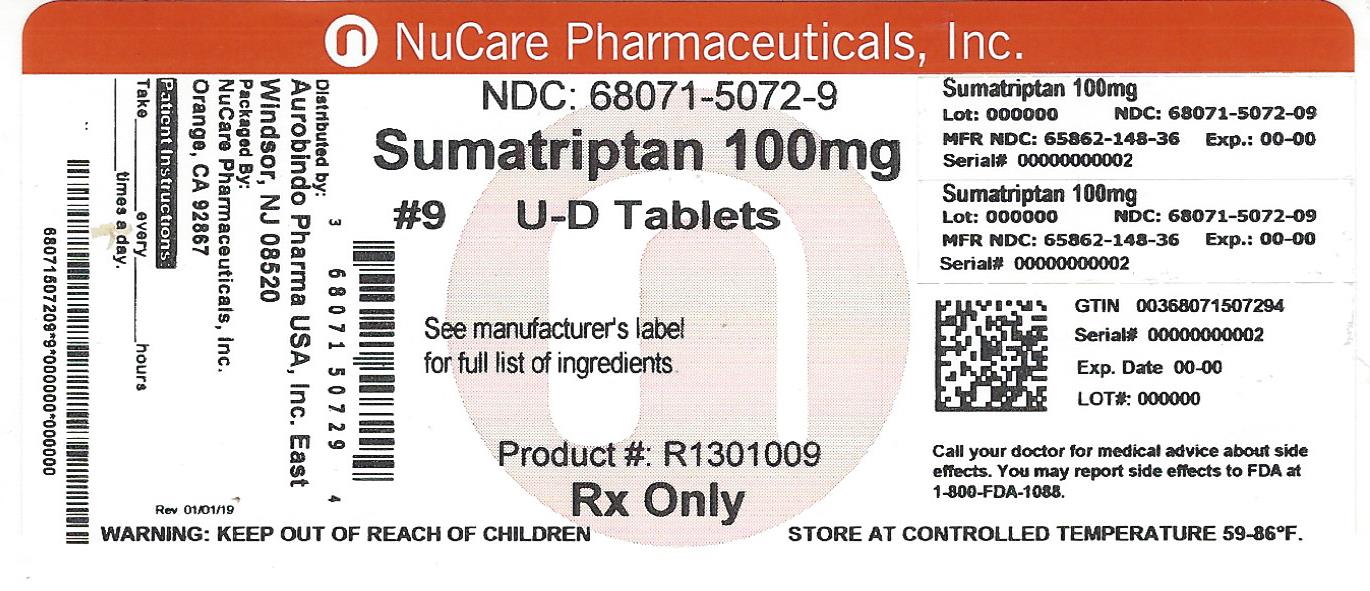 DRUG LABEL: Sumatriptan
NDC: 68071-5072 | Form: TABLET
Manufacturer: NuCare Pharmaceuticals,Inc.
Category: prescription | Type: HUMAN PRESCRIPTION DRUG LABEL
Date: 20240619

ACTIVE INGREDIENTS: SUMATRIPTAN SUCCINATE 100 mg/1 1
INACTIVE INGREDIENTS: CROSCARMELLOSE SODIUM; CALCIUM PHOSPHATE, DIBASIC, ANHYDROUS; MAGNESIUM STEARATE; MICROCRYSTALLINE CELLULOSE; POLYSORBATE 80; SODIUM BICARBONATE

MEDICATION GUIDE

Sumatriptan Succinate Tablets